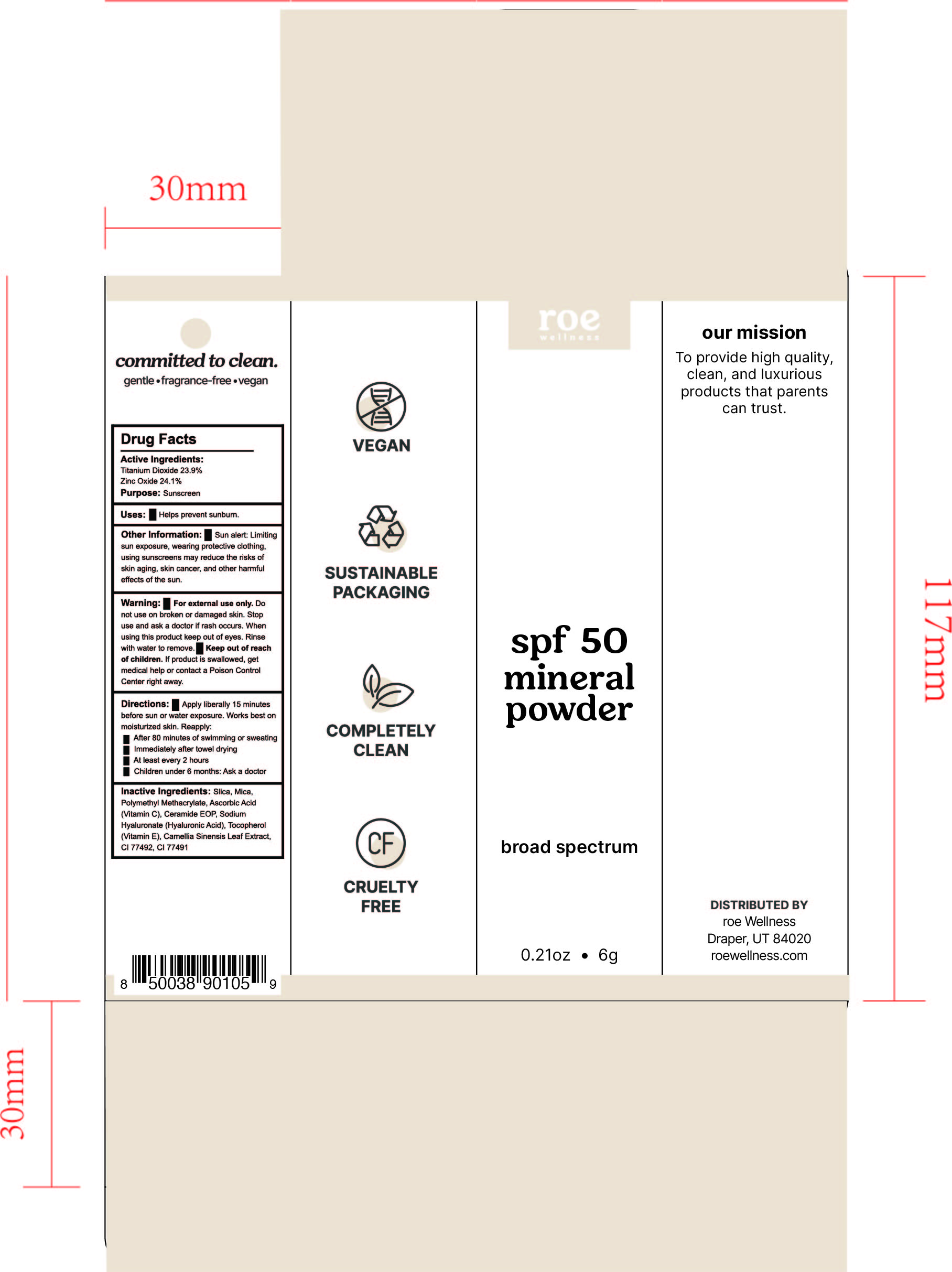 DRUG LABEL: spf 50 mineral powder sunscreen
NDC: 83369-001 | Form: POWDER
Manufacturer: Smalls Brand LLC DBA Roe Wellness
Category: otc | Type: HUMAN OTC DRUG LABEL
Date: 20260219

ACTIVE INGREDIENTS: TITANIUM DIOXIDE 23.9 g/100 g; ZINC OXIDE 24.1 g/100 g
INACTIVE INGREDIENTS: GREEN TEA LEAF; FERRIC OXIDE YELLOW; SILICON DIOXIDE; MICA; ASCORBIC ACID; CERAMIDE 1; TOCOPHEROL; HYALURONATE SODIUM; FERRIC OXIDE RED; POLY(METHYL METHACRYLATE; 450000 MW)

Roe Wellness Powder sunscreen

Active Ingredients:

Titanium DIoxide 23.9%

Zinc Oxide 24.1 %

Purpose: Sunscreen

Uses:

- Helps prevent sunburn

Keep out of reach of children. If product is swallowed, get medical help or contact a Poison Control Center right away.

Stop use and ask a doctor if rash occurs

Warning:

- For external use only. Do not use on broken or damaged skin
- When using this product keep out of eyes. Rinse with water to remove.

Directions:

- Apply liberally 15 minutes before sun or water exposure. Works best on moisturized skin. Reapply:
- After 80 minutes of swimming or sweating
- Immediately after towel drying
- At least every 2 hours
- Children under 6 months: Ask a doctor

INACTIVE INGREDIENT

Inactive ingredients: Silca, Mica, Polymethyl Methacrylate, Ascorbic Acid (Vitamin C), Ceramide EOP, Sodium Hyaluronate (Hyaluronic Acid), Tocopherol (Vitamin E), Camellia Sinensis Leaf Extract, CI 77492, CI 77491

PACKAGE LABEL

roe wellness

spf 50 mineral powder

borad spectrum

0.21 oz 6g